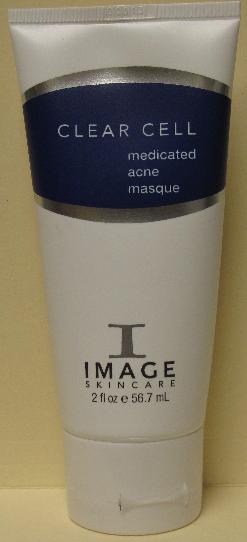 DRUG LABEL: Clear Cell Medicated Acne Masque
NDC: 62742-4044 | Form: CREAM
Manufacturer: Allure Labs, Inc.
Category: otc | Type: HUMAN OTC DRUG LABEL
Date: 20100723

ACTIVE INGREDIENTS: SALICYLIC ACID 50 mg/1 mL

Drug Facts

INDICATIONS AND USAGE SECTION:

An aha/bha blended acne masque designed to immediately draw out impurities and excess oil. Anti-oxidant blends of nutrients soothe irritated and red acne lesions. This amazing masque leaves skin fresh and oil-free.

Paraben-free

DIRECTIONS:

Apply to cleansed skin for 5-15 minutes, remove with tepid water, followed by a cold water splash. May be used as a spot treatment for active lesions.

INDICATIONS:

Acne and acne-prone skin

ACTIVE INGREDIENTS:
Salicylic Acid

INACTIVE INGREDIENTS:

Aqua (water), Magnesium Aluminum Silicate, Kaolin, Glycolic acid, Dimethyl Sulfone, Aloe vera gel, Glycerin, Sorbitol, Melaleuca alternifolia leaf oil (Tea Tree Oil), Sodium Polystyrene Sulfonate, Algae Extract, Cucumis sativus (Cucumber) fruit extract, Panthenol, Extracts of Malva sylvestris (Mallow), Mentha piperita (Peppermint Leaf), Primula veris, Alchemilla vulgaris, Veronica officinalis, Melissa officinalis leaf, Achillea millefolium, Titanium Dioxide, Sodium Hyaluronate, Caprylyl glycol and Phenoxyethanol and Hexylene glycol, Triethanolamine, Chamomilla recutita flower extract, Rosemarinus officinalis leaf extract, Melia azadirachta leaf extract, Camellia sinensis leaf extract , Hydrolyzed wheat protein, Spiraea ulmaria Flower Extract (and) Centella asiatica extract (and) amino acids, Xanthan Gum, Leptospermum scoparium oil (Manuka oil), Eucalyptus globulus leaf oil, Allantoin, Disodium EDTA.

PACKAGE LABEL

DISTRIBUTOR:

Image International

Palm Beach, FL 33411 USA

www.imageskincare.com

IMAGE OF PRINCIPAL DISPLAY PANEL: